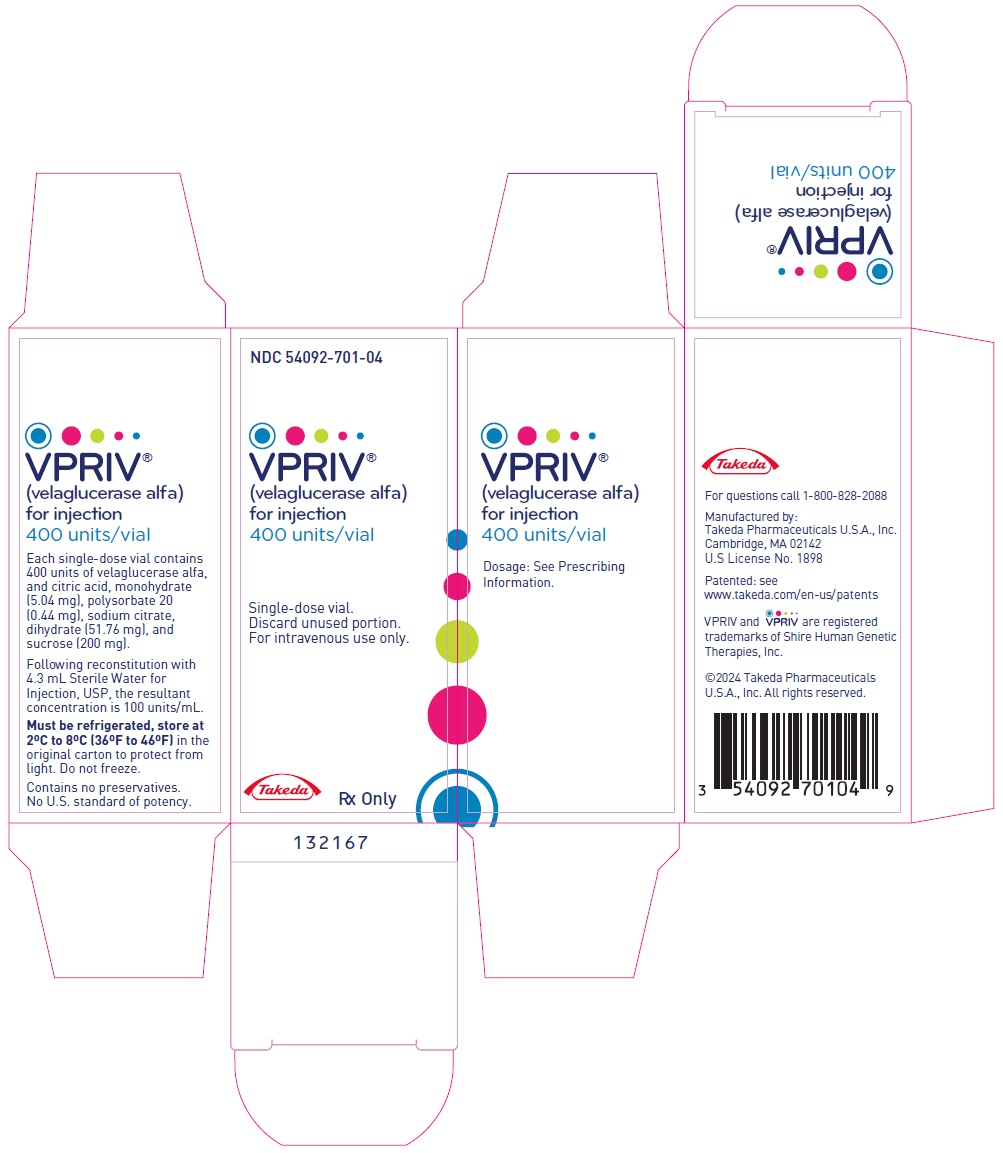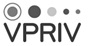 DRUG LABEL: VPRIV
NDC: 54092-701 | Form: INJECTION, POWDER, LYOPHILIZED, FOR SOLUTION
Manufacturer: Takeda Pharmaceuticals America, Inc.
Category: prescription | Type: HUMAN PRESCRIPTION DRUG LABEL
Date: 20241126

ACTIVE INGREDIENTS: VELAGLUCERASE ALFA 2.5 mg/1 mL
INACTIVE INGREDIENTS: CITRIC ACID MONOHYDRATE 1.26 mg/1 mL; POLYSORBATE 20 0.11 mg/1 mL; TRISODIUM CITRATE DIHYDRATE 12.94 mg/1 mL; SUCROSE 50 mg/1 mL

HIGHLIGHTS OF PRESCRIBING INFORMATION

These highlights do not include all the information needed to use VPRIV safely and effectively. See full prescribing information for VPRIV.
VPRIV® (velaglucerase alfa) for injection, for intravenous use
Initial U.S. Approval: 2010

WARNING: HYPERSENSITIVITY REACTIONS INCLUDING ANAPHYLAXIS

See full prescribing information for complete boxed warning.

- Anaphylaxis has occurred during the early course of enzyme replacement therapy and after extended duration of therapy. (5.1)
- Initiate VPRIV in a healthcare setting with appropriate medical monitoring and support measures, including access to cardiopulmonary resuscitation equipment. (5.1)
- If a severe hypersensitivity reaction (e.g., anaphylaxis) occurs, discontinue VPRIV and immediately initiate appropriate medical treatment, including use of epinephrine. (5.1)

RECENT MAJOR CHANGES

Boxed Warning | 7/2024
Dosage and Administration (2.1) | 7/2024
Warnings and Precautions (5.1) | 7/2024

1 INDICATIONS AND USAGE

VPRIV is a hydrolytic lysosomal glucocerebroside-specific enzyme indicated for long-term enzyme replacement therapy (ERT) for patients with type 1 Gaucher disease. (1)

2 DOSAGE AND ADMINISTRATION

- Administration of VPRIV should be supervised by a healthcare provider knowledgeable in the management of hypersensitivity reactions including anaphylaxis (2.1)
- Recommended Starting Dose in Adults and Pediatric Patients 4 Years of Age or Older:
  - Patients Naïve to Enzyme Replacement Therapy: 60 Units/kg (2.2)
  - Patients being treated with stable imiglucerase dosages for Gaucher disease: Can switch to VPRIV at previous imiglucerase dose two weeks after last imiglucerase dose (2.3)
- Determine number of vials to be reconstituted based on patient's actual weight and prescribed dose (2.4)
- Supplied VPRIV lyophilized powder must be reconstituted with Sterile Water for Injection (2.4)
- Reconstituted VPRIV solution must be diluted in 100 mL of 0.9% Sodium Chloride Injection prior to intravenous infusion (2.4)
- Administer the diluted VPRIV solution through an in-line low protein-binding 0.2 or 0.22 µm filter (2.5)

3 DOSAGE FORMS AND STRENGTHS

For injection: 400 units lyophilized powder single-dose vials (3)

4 CONTRAINDICATIONS

None (4)

5 WARNINGS AND PRECAUTIONS

See boxed warning (5.1)

6 ADVERSE REACTIONS

Most common adverse reactions (≥10%) are: hypersensitivity reactions, headache, dizziness, abdominal pain, nausea, back pain, joint pain, prolonged activated PTT, fatigue/asthenia, and pyrexia (6.1).

To report SUSPECTED ADVERSE REACTIONS, contact Takeda Pharmaceuticals at 1-800-828-2088 or FDA at 1-800-FDA-1088 or www.fda.gov/medwatch.

FULL PRESCRIBING INFORMATION

WARNING: HYPERSENSITIVITY REACTIONS INCLUDING ANAPHYLAXIS

Patients treated with enzyme replacement therapies have experienced life-threatening hypersensitivity reactions, including anaphylaxis. Anaphylaxis has occurred during the early course of enzyme replacement and after extended duration of therapy.

Initiate VPRIV in a healthcare setting with appropriate medical monitoring and support measures, including access to cardiopulmonary resuscitation equipment. If a severe hypersensitivity reaction (e.g., anaphylaxis) occurs, discontinue VPRIV and immediately initiate appropriate medical treatment, including use of epinephrine. Inform patients of the symptoms of life-threatening hypersensitivity reactions, including anaphylaxis and to seek immediate medical care should symptoms occur [see Warnings and Precautions (5.1)].

1 INDICATIONS AND USAGE

VPRIV is indicated for long-term enzyme replacement therapy (ERT) for patients with type 1 Gaucher disease.

2 DOSAGE AND ADMINISTRATION

2.1 Recommendations Prior to VPRIV treatment

Administration of VPRIV should be supervised by a healthcare provider knowledgeable in the management of hypersensitivity reactions including anaphylaxis [see Warnings and Precautions (5.1)].

Initiate VPRIV in a healthcare setting with appropriate medical monitoring and support measures, including access to cardiopulmonary resuscitation equipment [see Warnings and Precautions (5.1)].

2.2 Recommended Starting Dosage in Patients Naïve to Enzyme Replacement Therapy

The recommended starting VPRIV dosage in naïve adults and naïve pediatric patients 4 years of age and older is 60 Units/kg administered every other week as a 60-minute intravenous infusion. The dosage can be adjusted based on achievement and maintenance of each patient's therapeutic goals.

2.3 Switching from Imiglucerase to VPRIV

Adults and pediatric patients 4 years of age and older currently being treated on a stable dosage of imiglucerase for type 1 Gaucher disease may be switched to VPRIV by starting treatment with VPRIV at the previous imiglucerase dosage two weeks after the last imiglucerase dose. VPRIV should be administered under the supervision of a healthcare professional as a 60-minute intravenous infusion. The dosage can be adjusted based on achievement and maintenance of each patient's therapeutic goals.

2.4 Reconstitution of the VPRIV Lyophilized Powder

VPRIV is a lyophilized powder, which requires reconstitution and dilution, using sterile technique, prior to intravenous infusion. VPRIV should be prepared as follows:

(a) Determine the number of vials to be reconstituted based on the individual patient's weight and the prescribed dose.
(b) Inject 4.3 mL of Sterile Water for Injection, USP into a vial containing VPRIV lyophilized powder.
(c) Mix gently. DO NOT SHAKE. The reconstituted VPRIV solution will have a 100 Units/mL concentration (400 Units VPRIV in 4 mL of solution).
(d) If additional vials are needed, repeat steps (b) and (c).
(e) Visually inspect the reconstituted VPRIV solution in the vials. The solution should be clear to slightly opalescent and colorless. Do not use if the solution is discolored or if foreign particulate matter is present.
(f) With a single syringe, withdraw the calculated dose of drug from the appropriate number of vials. Using a separate syringe, withdraw air from a bag of 100 mL of 0.9% Sodium Chloride Injection suitable for intravenous administration. Then dilute the calculated dose of VPRIV directly into the 0.9% Sodium Chloride Injection. Mix gently. DO NOT SHAKE. Slight flocculation (described as white irregular shaped particles) may occasionally occur. Diluted solution with slight flocculation is acceptable for administration.
(g) Because VPRIV contains no preservatives, use the reconstituted VPRIV solution and the diluted VPRIV solution immediately. If immediate use is not possible, the reconstituted VPRIV solution or the diluted VPRIV solution may be stored for up to 24 hours at 2ºC to 8ºC (36ºF to 46ºF). Do not freeze and protect from light. Complete the infusion within 24 hours of reconstitution of vials.
(h) Vials are for one-time use and only for one patient. Discard any unused solution.

2.5 Important Administration Instructions

Administer the diluted VPRIV solution through an in-line low protein-binding 0.2 or 0.22 µm filter over 60 minutes. Do not infuse VPRIV with other products in the same infusion tubing because the compatibility of a VPRIV solution with other products has not been evaluated.

2.6 Premedication to Reduce Risk of Subsequent Hypersensitivity Reactions

Consider pre-treatment with antihistamines and/or corticosteroids in patients who exhibited symptoms of hypersensitivity associated with prior velaglucerase alfa product infusions. Appropriate medical support should be readily available when VPRIV is administered [see Warnings and Precautions (5.1)].

3 DOSAGE FORMS AND STRENGTHS

For injection: 400 units of a sterile, white to off-white, lyophilized powder in single-dose vials for reconstitution and dilution.

4 CONTRAINDICATIONS

None.

5 WARNINGS AND PRECAUTIONS

5.1 Hypersensitivity Reactions Including Anaphylaxis

Life-threatening hypersensitivity reactions, including anaphylaxis, have occurred in patients treated with enzyme replacement therapies, including VPRIV. VPRIV-treated patients have had these reactions occur in clinical studies and postmarketing experience [see Adverse Reactions (6.1) and Clinical studies (14)]. Hypersensitivity reactions were the most commonly observed adverse reactions in patients treated with VPRIV in clinical studies. Patients were not routinely pre-medicated prior to infusion of VPRIV during clinical studies. The most commonly observed symptoms of hypersensitivity reactions were: headache, dizziness, hypotension, hypertension, nausea, fatigue/asthenia, and pyrexia/body temperature increased. Generally the reactions were mild and, in treatment-naïve patients, onset occurred mostly during the first 6 months of treatment and tended to occur less frequently with time. Additional hypersensitivity reactions of chest discomfort, dyspnea, pruritus and vomiting have been reported in post-marketing experience.

Anaphylaxis has occurred during the early course of enzyme replacement therapy and after extended duration of therapy. Administration of VPRIV should be supervised by a healthcare provider knowledgeable in the management of hypersensitivity reactions including anaphylaxis. Initiate VPRIV in a healthcare setting with appropriate medical monitoring and support measures, including access to cardiopulmonary resuscitation equipment.

The management of hypersensitivity reactions should be based on the severity of the reaction, e.g., slowing the infusion rate, treatment with medications such as antihistamines, antipyretics and/or corticosteroids, and/or stopping and resuming treatment with increased infusion time. If a severe hypersensitivity reaction (e.g., anaphylaxis) occurs, discontinue VPRIV and immediately initiate appropriate medical treatment, including use of epinephrine.

In cases where patients have exhibited symptoms of hypersensitivity to velaglucerase alfa or excipients in the drug product or to other enzyme replacement therapy, pre-treatment with antihistamines and/or corticosteroids may prevent subsequent reactions. Inform patients of the symptoms of life-threatening hypersensitivity reactions, including anaphylaxis and to seek immediate medical care should symptoms occur.

6 ADVERSE REACTIONS

6.1 Clinical Trials Experience

Because clinical trials are conducted under widely varying conditions, adverse reaction rates observed in the clinical trials of a drug cannot be directly compared to rates in the clinical trials of another drug and may not reflect the rates observed in practice.

The data described below reflect exposure of 94 patients with type 1 Gaucher disease who received VPRIV at doses ranging from 15 Units/kg to 60 Units/kg every other week in 5 clinical studies. Fifty-four (54) patients were naïve to enzyme replacement therapy (ERT) and received VPRIV for 9 months and 40 patients switched from imiglucerase to VPRIV treatment and received VPRIV for 12 months [see Clinical Studies (14)]. Patients were between 4 and 71 years old at time of first treatment with VPRIV, and included 46 male and 48 female patients.

The most serious adverse reactions in patients treated with VPRIV were hypersensitivity reactions [see Warnings and Precautions (5.1)].

The most commonly reported adverse reactions (occurring in ≥10% of patients) that were considered related to VPRIV are shown in Table 1. The most common adverse reactions were hypersensitivity reactions.

Table 1: Adverse Reactions Observed in ≥10% of Adult and Pediatric Patients with Type 1 Gaucher Disease Treated with VPRIV in the Pooled 5 Clinical Studies
Adverse Reaction | Naïve to ERT N = 54 Number of patients (%) | Switched from imiglucerase to VPRIV N = 40 Number of patients (%)
Hypersensitivity reaction [Denotes any event considered related to and occurring within up to 24 hours of VPRIV infusion, including one case of anaphylaxis.] | 28 (52) | 9 (23)
Headache | 19 (35) | 12 (30)
Dizziness | 12 (22) | 3 (8)
Pyrexia | 12 (22) | 5 (13)
Abdominal pain | 10 (19) | 6 (15)
Back pain | 9 (17) | 7 (18)
Joint pain (knee) | 8 (15) | 3 (8)
Asthenia/Fatigue | 8 (15) | 5 (13)
Activated partial thromboplastin time prolonged | 6 (11) | 2 (5)
Nausea | 3 (6) | 4 (10)

Less common adverse reactions affecting more than one patient (>2% in the treatment-naïve group and >3% in patients switched from imiglucerase to VPRIV treatment) were bone pain, tachycardia, rash, urticaria, flushing, hypertension, and hypotension.

Adverse Reactions in Pediatric Patients

The safety profile of VPRIV was similar between pediatric patients (ages 4 to 17 years) and adult patients. Adverse reactions more commonly seen in pediatric patients compared to adult patients include (>10% difference): rash, aPTT prolonged, and pyrexia.

6.2 Immunogenicity

As with all therapeutic proteins, there is a potential for immunogenicity. The detection of antibody formation is highly dependent on the sensitivity and specificity of the assay. Additionally, the observed incidence of antibody (including neutralizing antibody) positivity in an assay may be influenced by several factors, including assay methodology, sample handling, timing of sample collection, concomitant medications, and underlying disease. For these reasons, comparison of the incidence of antibodies to VPRIV in the studies described below with the incidence of antibodies in other studies or to other products may be misleading.

In clinical studies, 1 of 54 (2%) enzyme treatment-naïve patients treated with VPRIV developed IgG antibodies to VPRIV. One additional patient developed IgG antibodies to VPRIV during an extension study. In both patients, the IgG antibodies to VPRIV were determined to be neutralizing in an in vitro assay. The presence of IgG antibodies to VPRIV was not associated with hypersensitivity reactions. It is unknown if the presence of IgG antibodies to VPRIV is associated with a higher risk of infusion reactions. Patients with an immune response to other enzyme replacement therapies who are switching to VPRIV should continue to be monitored for antibodies to VPRIV.

6.3 Postmarketing Experience

The following adverse reactions have been identified during post-approval use of VPRIV. Because these reactions are reported voluntarily from a population of uncertain size, it is not always possible to reliably estimate their frequency or establish a causal relationship to drug exposure.

Gastrointestinal disorders: vomiting (in some cases vomiting can be serious, requiring hospitalization and/or drug discontinuation)

8 USE IN SPECIFIC POPULATIONS

8.1 Pregnancy

Risk Summary

Available data on use of velaglucerase alfa in pregnant women includes more than 300 pregnancies reported from the pharmacovigilance database and published observational cohort studies, including the international Gaucher Disease registry. While available data cannot definitively establish or exclude the absence of a velaglucerase alfa associated risk during pregnancy, these data have not identified an association with use of velaglucerase alfa during pregnancy and major birth defects, miscarriage, or adverse maternal or fetal outcomes. In animal reproduction studies no fetal harm was observed in rats or rabbits when velaglucerase alfa was administered intravenously during organogenesis at doses with exposures up to 1.8 times and 4.3 times, respectively, the recommended human daily dose (see Data).

The estimated background risk of major birth defects and miscarriage for the indicated population is unknown. All pregnancies have a background risk of major birth defects, loss, and other adverse outcomes. In the U.S. general population, the estimated major birth defects and miscarriage in clinically recognized pregnancies is 2 to 4% and 15 to 20%, respectively.

Clinical Considerations

Disease-Associated Maternal and Embryo/Fetal Risk

Women with Type 1 Gaucher disease have an increased risk of spontaneous abortion, especially if disease symptoms are not treated and controlled pre-conception and during a pregnancy. Pregnancy may exacerbate existing Type 1 Gaucher disease symptoms or result in new disease manifestations. Type 1 Gaucher disease manifestations may lead to adverse pregnancy outcomes including hepatosplenomegaly which can interfere with the normal growth of a pregnancy, and thrombocytopenia which can lead to excessive bleeding.

Data

Animal Data

Embryo-fetal development studies with velaglucerase alfa have been performed during the period of organogenesis in pregnant rats (gestation days 7 through 17) and rabbits (gestation days 6 through 18). In pregnant rats intravenous doses up to 17 mg/kg (102 mg/m^2, about 1.8 times the recommended human dose of 60 Units/kg or 1.5 mg/kg or 55.5 mg/m^2 based on the body surface area) were administered two to three times weekly. In pregnant rabbits intravenous doses up to 20 mg/kg (240 mg/m^2, about 4.3 times the recommended human dose of 60 Units/kg based on the body surface area) were administered two to three times weekly. These studies did not reveal any evidence of impaired fertility or harm to the fetus due to velaglucerase alfa.

In a pre- and postnatal development study, velaglucerase alfa was administered intravenously to pregnant rats twice weekly from gestation day 6 to lactation day 19. There was no evidence of any adverse effect on pre- and postnatal development at doses up to 17 mg/kg/day (102 mg/m^2, about 1.8 times the recommended human dose of 60 Units/kg based on the body surface area).

8.2 Lactation

Risk Summary

There are no data available on the presence of velaglucerase alfa in human milk. The reported cases from the pharmacovigilance database are insufficient to determine any effects on the breastfed infant or on milk production. Endogenous beta-glucocerebrosidase is present in human milk. The developmental and health benefits of breastfeeding should be considered along with the mother's clinical need for VPRIV and any potential adverse effects on the breastfed child from VPRIV or from the underlying maternal condition.

8.4 Pediatric Use

The safety and effectiveness of VPRIV have been established for enzyme replacement therapy (ERT) in patients between 4 and 17 years of age with type 1 Gaucher disease. Use of VPRIV in this age group is supported by evidence from adequate and well-controlled studies of VPRIV in 74 adult patients and 20 pediatric patients. The safety and efficacy profiles were similar between pediatric and adult patients [see Adverse Reactions (6.1), Clinical Studies (14)]. The efficacy and safety of VPRIV has not been established in pediatric patients younger than 4 years of age.

8.5 Geriatric Use

In clinical studies of VPRIV in Gaucher's disease, a total of 56 VPRIV-treated patients were 65 years of age or older including 10 patients who were 75 years of age or older. Among 205 patients who switched from imiglucerase to VPRIV, 52 patients were 65 years of age or older of which 10 were 75 years and older. The adverse reaction profile in elderly patients was consistent with that previously observed across pediatric and adult patients. Other reported clinical experience has not identified differences in responses between the elderly and younger patients. In general, dose selection for an elderly patient should be approached cautiously, considering potential comorbid conditions.

11 DESCRIPTION

Velaglucerase alfa is a hydrolytic lysosomal glucocerebroside-specific enzyme produced by gene activation technology in a human fibroblast cell line. Velaglucerase alfa is a glycoprotein of 497 amino acids and a molecular weight of approximately 63 kDa. Velaglucerase alfa has the same amino acid sequence as the naturally occurring human enzyme, glucocerebrosidase. Velaglucerase alfa contains five potential N-linked glycosylation sites; four of these sites are occupied by glycan chains. Velaglucerase alfa contains predominantly high mannose-type N-linked glycan chains. The high mannose type N-linked glycan chains are specifically recognized and internalized via the mannose receptor present on the surface on macrophages, the cells that accumulate glucocerebroside in Gaucher disease.

VPRIV is dosed by units/kg, where one unit of enzyme activity is defined as the quantity of enzyme required to convert one micromole of p-nitrophenyl ß-D-glucopyranoside to p-nitrophenol per minute at 37ºC.

VPRIV (velaglucerase alfa) for injection is supplied as a sterile, preservative free, white to off-white lyophilized powder in single-dose vials for intravenous infusion after reconstitution and dilution. Each single-dose vial contains 400 units of velaglucerase alfa, and citric acid, monohydrate (5.04 mg), polysorbate 20 (0.44 mg), sodium citrate, dihydrate (51.76 mg), and sucrose (200 mg). After reconstitution with 4.3 mL Sterile Water for Injection, USP, the final concentration is 100 units/mL with a pH of approximately 6.0.

12 CLINICAL PHARMACOLOGY

12.1 Mechanism of Action

Gaucher disease is an autosomal recessive disorder caused by mutations in the GBA gene, which results in a deficiency of the lysosomal enzyme beta-glucocerebrosidase. Glucocerebrosidase catalyzes the conversion of the sphingolipid glucocerebroside into glucose and ceramide. The enzymatic deficiency causes an accumulation of glucocerebroside primarily in the lysosomal compartment of macrophages, giving rise to foam cells or "Gaucher cells". Velaglucerase alfa catalyzes the hydrolysis of glucocerebroside, reducing the amount of accumulated glucocerebroside. In clinical trials VPRIV reduced spleen and liver size, and improved anemia and thrombocytopenia.

In this lysosomal storage disorder (LSD), clinical features are reflective of the accumulation of Gaucher cells in the liver, spleen, bone marrow, and other organs. The accumulation of Gaucher cells in the liver and spleen leads to organomegaly. Presence of Gaucher cells in the bone marrow and spleen lead to clinically significant anemia and thrombocytopenia.

12.3 Pharmacokinetics

In a multicenter study conducted in pediatric (N=7, 4 to 17 years old) and adult (N=15, 19 to 62 years old) patients with type 1 Gaucher disease, pharmacokinetic evaluations were performed at Weeks 1 and 37 following 60-minute intravenous infusions of VPRIV 60 Units/kg every other week. Serum velaglucerase alfa concentrations declined rapidly with a mean half life of 11 to 12 minutes. The mean velaglucerase alfa clearance ranged from 6.72 to 7.56 mL/min/kg. The mean volume of distribution at steady state ranged from 82 to 108 mL/kg (8.2% to 10.8% of body weight).

No accumulation or change in velaglucerase alfa pharmacokinetics over time from Weeks 1 to 37 was observed upon multiple-dosing 60 Units/kg every other week.

Based on the limited data, there were no notable pharmacokinetic differences between male and female patients in this study. The effect of age on pharmacokinetics of velaglucerase alfa was inconclusive.

The effect of anti-drug antibody formation on the pharmacokinetic parameters of velaglucerase alfa is unknown.

13 NONCLINICAL TOXICOLOGY

13.1 Carcinogenesis, Mutagenesis, Impairment of Fertility

Long-term studies in animals to evaluate carcinogenic potential or studies to evaluate mutagenic potential have not been performed with velaglucerase alfa.

In a fertility study in male and female rats, velaglucerase alfa did not cause any significant adverse effect on male or female fertility parameters up to a maximum intravenous dose of 17 mg/kg (102 mg/m^2, about 1.8 times the recommended human dose of 60 Units/kg based on the body surface area).

14 CLINICAL STUDIES

14.1 Overview of Clinical Studies of VPRIV for Gaucher Disease

The efficacy of VPRIV was assessed in three clinical trials in a total of 99 patients with type 1 Gaucher disease: 82 patients age 4 years and older received VPRIV and 17 patients age 3 years and older received imiglucerase. Studies I and II were conducted in patients who were not currently receiving Gaucher disease-specific therapy. Study III was conducted in patients who were receiving imiglucerase treatment immediately before starting VPRIV. The long-term safety of VPRIV was assessed in Study IV, an open-label extension trial in a total of 93 patients with type 1 Gaucher disease ages 3 years and older. Patients who had completed Studies I to III were eligible to participate in Study IV. In Studies I through IV, VPRIV was administered intravenously over 60 minutes at a maximum dose of 60 Units/kg every other week. Doses above 60 Units/kg were not studied in these trials.

14.2 Clinical Trials of VPRIV as Initial Therapy

Study I was a 12-month, randomized, double-blind, parallel-dose-group, multinational trial in 25 patients age 4 years and older with Gaucher disease-related anemia and either thrombocytopenia or organomegaly. Patients were not allowed to have had disease-specific therapy for at least the previous 30 months; all but one had no prior therapy. The mean age was 26 years and 60% were male. Patients were randomized to receive VPRIV at a dose of either 45 Units/kg (N=13) or 60 Units/kg (N=12) every other week. The recommended starting dose in naïve patients is 60 Units/kg. The 45 Units/kg dosage is not recommended as a starting dose in naïve patients [see Dosage and Administration (2.1)].

At baseline, mean hemoglobin concentration was 10.6 g/dL, mean platelet count was 97 × 10^9/L, mean liver volume was 3.6 % of body weight (% BW), and mean spleen volume was 2.9 % BW.

For all studies, liver and spleen volumes were measured by MRI. The changes in clinical parameters after 12 months of treatment are shown in Table 2. The observed change from baseline in the primary endpoint, hemoglobin concentration, was considered to be clinically meaningful in the 60 Units/kg dose, in light of the natural history of untreated Gaucher disease.

Table 2: Mean Change from Baseline to Month 12 for Clinical Parameters in Patients with Type 1 Gaucher Disease Initiating Therapy with VPRIV Given Every Other Week in Study I
Clinical Parameter | VPRIV 45 Units/kg [The recommended starting dose in naïve patients is 60 Units/kg. The 45 Units/kg dosage is not recommended as a starting dose in naïve patients [see Dosage and Administration (2.1)].] N = 13 Mean ± SE | VPRIV 60 Units/kg N = 12 Mean ± SE
Hemoglobin concentration change (g/dL) | 2.4 ± 0.4 [Statistically significant changes from baseline after adjusting for performing multiple tests] | 2.4 ± 0.3 [Primary study endpoint was hemoglobin concentration change in the 60 Units/kg group, p<0.001]
Platelet count change (× 10^9/L) | 41 ± 14 | 51 ± 12
Liver volume change (% BW) | -0.30 ± 0.29 | -0.84 ± 0.33
Spleen volume change (% BW) | -1.9 ± 0.6 | -1.9 ± 0.5
SE = standard error of the mean

Study II was a 9-month, randomized, double-blind, active-controlled (imiglucerase), parallel-group, multinational study in 34 patients age 4 years and older. Patients were required to have Gaucher disease-related anemia and either thrombocytopenia or organomegaly. Patients were not allowed to have had disease-specific therapy for at least the previous 12 months. The mean age was 30 years and 53% were female; the youngest patient who received VPRIV was age 4 years. Patients were randomized to receive either 60 Units/kg of VPRIV (N=17) or 60 Units/kg of imiglucerase (N=17) every other week.

At baseline, the mean hemoglobin concentration was 11.0 g/dL, mean platelet count was 171 × 10^9/L, and mean liver volume was 4.3 % BW. For the patients who had not had splenectomy (7 in each group) the mean spleen volume was 3.4 % BW. After 9 months of treatment, the mean absolute increase from baseline in hemoglobin concentration was 1.6 g/dL ± 0.2 (SE) for patients treated with VPRIV. The mean treatment difference in change from baseline to 9 months [VPRIV – imiglucerase] was 0.1 g/dL ± 0.4 (SE).

In both studies, examination of age and gender subgroups did not identify differences in response to VPRIV among these subgroups. The number of non-Caucasian patients in these studies was too small to adequately assess any difference in effects by race.

In Study IV, treatment naïve patients were administered VPRIV. Treatment-naïve patients continued to show improvements in clinical parameters (hemoglobin concentration, platelet count, liver volume, and spleen volume) compared with baseline for up to 60 months of treatment with ERT.

14.3 Clinical Trial in Patients Switching from Imiglucerase Treatment to VPRIV

Study III was a 12-month, open-label, single-arm, multinational study in 40 patients age 9 years and older who had been receiving treatment with imiglucerase at doses ranging between 15 Units/kg to 60 Units/kg for a minimum of 30 consecutive months. Patients also were required to have a stable biweekly dose of imiglucerase for at least 6 months prior to enrollment. The mean age was 36 years and 55% were female. Imiglucerase therapy was stopped, and treatment with VPRIV was administered every other week at the same number of units as the patient's previous imiglucerase dose. Adjustment of dosage was allowed by study criteria if needed in order to maintain clinical parameters [see Dosage and Administration (2.2)].

Hemoglobin concentrations and platelet counts remained stable on average through 12 months of VPRIV treatment. After 12 months of treatment with VPRIV the median hemoglobin concentration was 13.5 g/dL (range: 10.8, 16.1) vs. the baseline value of 13.8 g/dL (range: 10.4, 16.5), and the median platelet count after 12 months was 174 × 10^9/L (range: 24, 408) vs. the baseline value of 162 × 10^9/L (range: 29, 399). No patient required dosage adjustment during the 12-month treatment period.

In Study IV, patients who had previously been receiving imiglucerase treatment were administered VPRIV. Patients previously treated with imiglucerase maintained stability in clinical parameters (hemoglobin concentration, platelet count, liver volume, and spleen volume) compared with baseline for up to 60 months of treatment with ERT.

16 HOW SUPPLIED/STORAGE AND HANDLING

How Supplied

VPRIV (velaglucerase alfa) for injection is a sterile, preservative free, white to off-white lyophilized powder requiring reconstitution and further dilution prior to use. It is supplied in individually packaged single-dose glass vials, which are closed with a butyl rubber stopper with a fluoro-resin coating and are sealed with an aluminum overseal with a flip-off plastic cap. VPRIV is available as: 400 units/vial (NDC 54092-701-04).

Storage

Store VPRIV refrigerated at 2ºC to 8ºC (36ºF to 46ºF) in the original carton to protect from light. Do not freeze. Do not use VPRIV after the expiration date on the vial.

17 PATIENT COUNSELING INFORMATION

Hypersensitivity Reactions Including Anaphylaxis

Advise patients of the following:

- Life-threatening hypersensitivity reactions, including anaphylaxis may occur with VPRIV treatment.
- Anaphylaxis has occurred during the early course of enzyme replacement therapy and after extended duration of therapy.
- Symptoms of life-threatening hypersensitivity reactions, including anaphylaxis and to seek immediate medical care should symptoms occur [see Warnings and Precautions (5.1)].

Manufactured by:

Takeda Pharmaceuticals U.S.A., Inc.
Cambridge, MA 02142
US License Number: 1898

VPRIV and are registered trademarks of Shire Human Genetic Therapies, Inc.

©2024 Takeda Pharmaceuticals U.S.A., Inc. All rights reserved.

Patented: see www.takeda.com/en-us/patents

VPR356

PRINCIPAL DISPLAY PANEL - 400 Unit Vial Box

NDC 54092-701-04

VPRIV®
(velaglucerase alfa)
for injection
400 units/vial

Single-dose vial.
Discard unused portion.
For intravenous use only.

Takeda

Rx Only